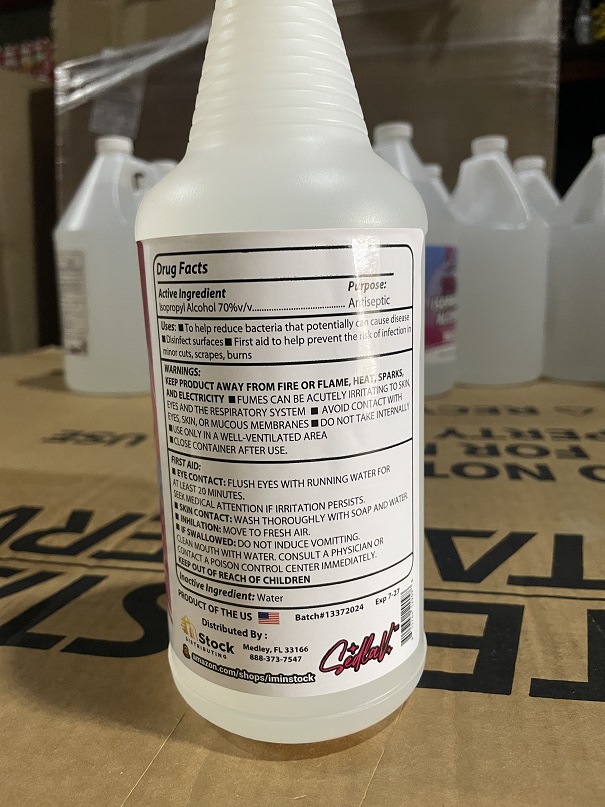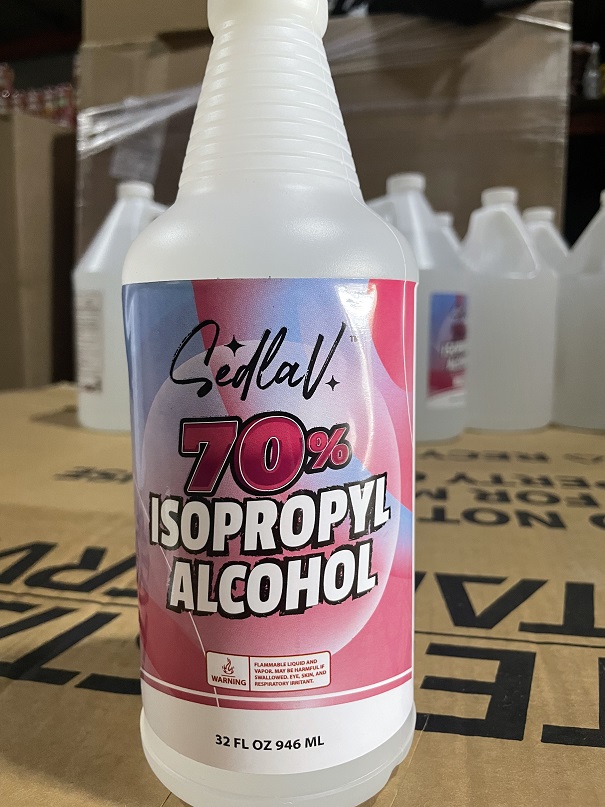 DRUG LABEL: SEDLAV
NDC: 84361-0003 | Form: LIQUID
Manufacturer: Instock Distributing
Category: otc | Type: HUMAN OTC DRUG LABEL
Date: 20251015

ACTIVE INGREDIENTS: ISOPROPYL ALCOHOL 669 mL/946 mL
INACTIVE INGREDIENTS: WATER

SEDLAV 70% ISOPROPYL ALCOHOL

Active Ingredient

Active Ingredient Isopropyl Alcohol 70% v/v Purpose: Antiseptic

Uses

To help reduce bacteria that potentially can cause disease

Disinfect surfaces

First aid to help prevent the risk of infection in minor cuts, scrapes, burns

Warnings

Keep product away from fire or flame, heat , sparks, and electricity

Fumes Can be acutely irritating to skin, eyes, and the respiratory system

Avoid contact wtih eyes, skin, or mucous membranes

Do not take internally

Use only in a well ventilated area

Close Container after use

First Aid

Eye Contact: Flush eyes with running water for 2 at least 20 minutes

Skin Contact: Wash thoroughly with soap and water.

Inhilation: Move to fresh air.

If swallowed: Do not induce vomitting. Clean mouth with water, consult a physician or contact a poison control center immediately.

KEEP OUT OF REACH OF CHILDREN

Inactive Ingredient

Inactive Ingredient: Water

Purpose:
Antiseptic

Uses: To help reduce bacteria that potentially can cause disease Disinfect surfaces

OTC is Keep Out of Reach of Children

PURPOSE

Uses: To help reduce bacteria that potentially can cause disease Disinfect surfaces

Purpose:
Antiseptic

Front Label

SEDLAV 70% Isopropyl Alcohol

32 FL OZ 946 mL

Warning:

Flammable Liquid And Vapor, May be harmful if swallowed, Eye,skin, and respiratory irritant.